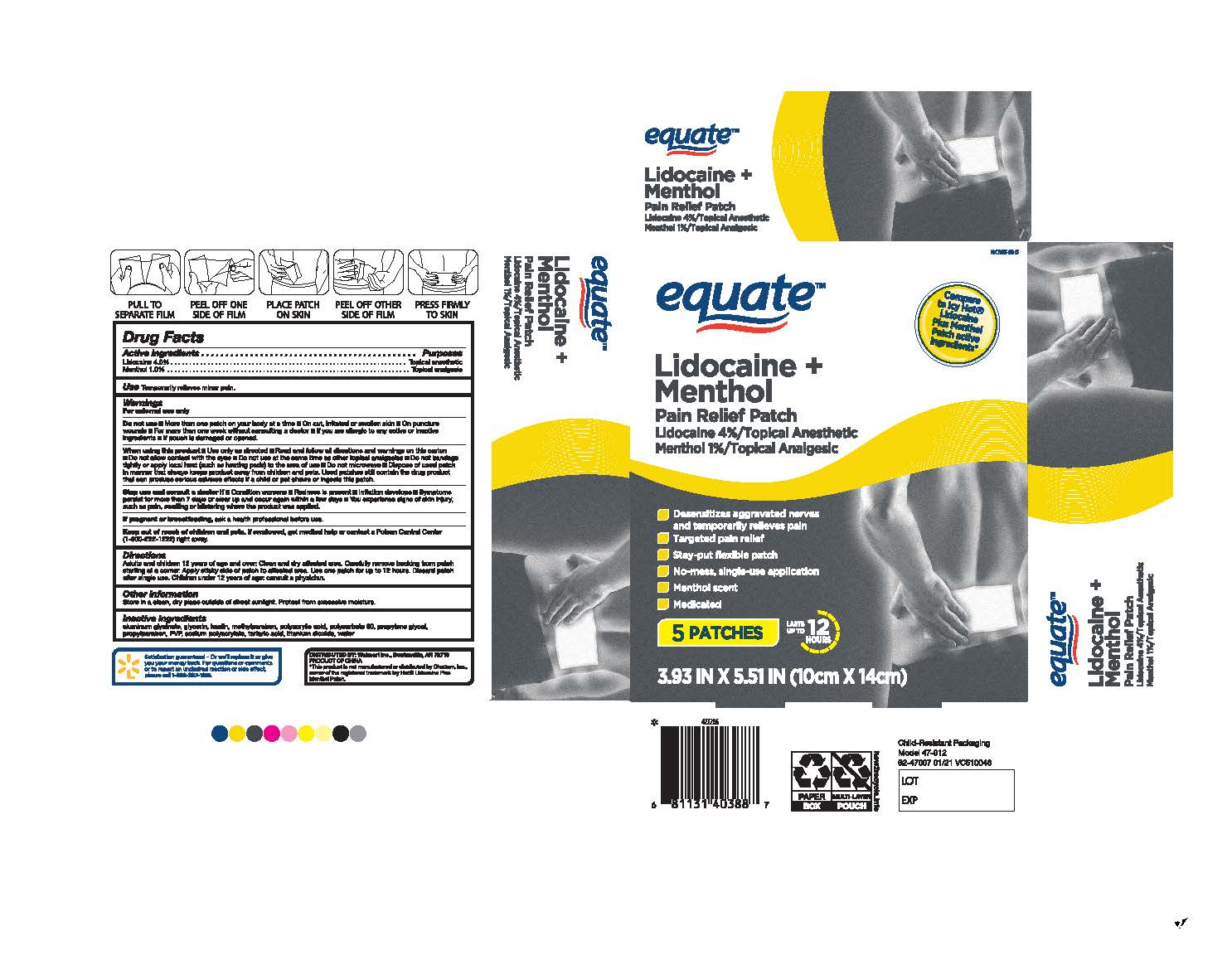 DRUG LABEL: Equate Lidocaine Cool and Heat
NDC: 79903-038 | Form: PATCH
Manufacturer: Walmart Stores Inc
Category: otc | Type: HUMAN OTC DRUG LABEL
Date: 20251227

ACTIVE INGREDIENTS: MENTHOL 1 g/100 g; LIDOCAINE 4 g/100 g
INACTIVE INGREDIENTS: GLYCERIN; POLYACRYLIC ACID (250000 MW); DIHYDROXYALUMINUM AMINOACETATE ANHYDROUS; KAOLIN; POLYSORBATE 80; PROPYLENE GLYCOL; POVIDONE, UNSPECIFIED; METHYLPARABEN; PROPYLPARABEN; SODIUM POLYACRYLATE (8000 MW); TARTARIC ACID; TITANIUM DIOXIDE; WATER

Equate Lidocaine Cool and Heat Patch 5 ct

ACTIVE INGREDIENT

Lidocaine 4.0%
Menthol 1.0%

PURPOSE

Topical Anesthetic
Topical Anesthetic

Uses

Temporarily relieves minor pain

- Warnings

For external use only.

WHEN USING

Use only as directed
Read and follow all directions and warnings on this carton
Do not allow contact with the eyes
Do not use at the same time as other topical analgesics
Do not bandage tightly or apply local heat (such as heating pads) to the area of use
Do not microwave
Dispose of the used patch in a manner that always keeps product away from children and pets. Used patches still contain the drug product that can produce serious adverse effects if a child or pet chews or ingests this patch.

DO NOT USE

More than one patch on your body at a time.
On cut, irritated or swollen skin
On puncture wounds
For more than one week without consulting a doctor
If you are allergic to any active or inactive ingredients
If pouch is damaged or opened

Stop and ask a doctor

Condition worsens
Redness is present
Irritation develops
Symptoms persist for more than 7 days or clear up and occur again within a few days
You experience signs of skin injury, such as pain, swelling or blistering where the product was applied

If pregnant or breastfeeding

Ask a health professional before use

Keep out of reach of children and pets

If swallowed, get medical help or contact a Poison Control Center (1800-222-1222) right away

Directions

Adults and children 12 years of age and over: Clean and the dry affected area. Carefully remove backing from the patch starting at a corner. Apply the sticky side of patch to the affected area. Use one patch for up to 12 hours. Discard patch after a single use. Children under 12 years old of age: consult a physician.

OTHER SAFETY INFORMATION

Store in a clean, dry place outside of direct sunlight. Protect for excessive moisture.

INACTIVE INGREDIENT

Aluminum glycinate, glycerin, kaolin, methylparaben, polyacrylic acid, polysorbate 80, propylene glycol, propylparaben, PVP, sodium polyacrylate, tartaric acid, titanium dioxide, water